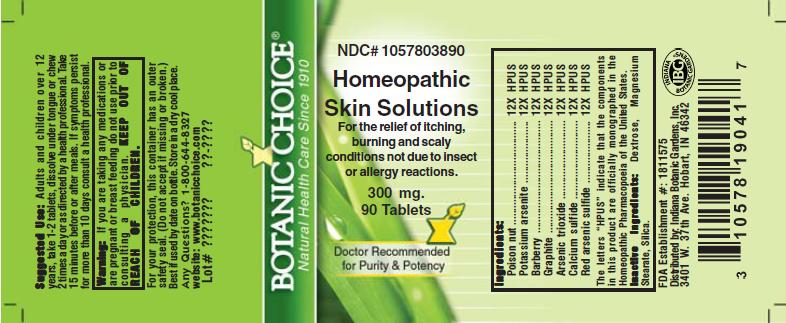 DRUG LABEL: Homeopathic Skin Solutions Formula
NDC: 10578-038 | Form: TABLET
Manufacturer: Indiana Botanic Gardens
Category: homeopathic | Type: HUMAN OTC DRUG LABEL
Date: 20110325

ACTIVE INGREDIENTS: STRYCHNOS NUX-VOMICA SEED 12 [hp_X]/1 1; POTASSIUM ARSENITE ANHYDROUS     12 [hp_X]/1 1; BERBERIS VULGARIS ROOT BARK 12 [hp_X]/1 1; GRAPHITE 12 [hp_X]/1 1; ARSENIC TRIOXIDE 12 [hp_X]/1 1; CALCIUM SULFIDE 12 [hp_X]/1 1; TETRAARSENIC TETRASULFIDE 12 [hp_X]/1 1
INACTIVE INGREDIENTS: DEXTROSE; MAGNESIUM STEARATE ; SILICON DIOXIDE 

Homeopathic Skin Solutions Formula

ACTIVE INGREDIENT

I n g r e d i e n t s :

Poison nut................................ 12X HPUS
Potassium arsenite............................ 12X HPUS
Barberry......................... 12X HPUS
Graphite.................................... 12X HPUS
Arsenic trioxide......................... 12X HPUS
Calcium sulfide............ 12X HPUS
Red arsenic sulfide........ 12X HPUS

The letters “HPUS” indicate that the components in
this product are officially monographed in the
Homeopathic Pharmacopoeia of the United States.

PURPOSE

For the relief of itching, burning and scaly conditions not due to insect or allergy conditions

KEEP OUT OF
REACH OF CHILDREN.

INDICATIONS AND USAGE

For the relief of itching, burning and scaly conditions not due to insect or allergy conditions

WARNINGS

Warning: If you are taking any medications or
are pregnant or breast feeding do not use prior to
consulting a physician.

DOSAGE AND ADMINISTRATION

Suggested Use: Adults and children over 12
years, take 1-2 tablets, dissolve under tongue or
chew 2 times a day or as directed by a health care
professional. Take 15 minutes before or after meals.
If symptoms persist for more than 10 days consult a
health professional.

Inactive Ingredients: Dextrose, Magnesium
Stearate, Silica.

PACKAGE LABEL

NDC# 1057803890

Homeopathic Skin Solutions Formula

For the relief of itching, burning and scaly conditions not due to insect or allergy conditions

300 mg.
90 Tablets

USER SAFETY WARNINGS

For your protection, this container has an outer
safety seal. (Do not accept if missing or broken.)
Best if used by date on bottle. Store in a dry cool place.
Any Questions? 1-800-644-8327
website: www.botanicchoice.com

FDA Establishment #: 1811575

Distributed by: Indiana Botanic Gardens, Inc.
3401 W. 37th Ave. Hobart, IN 46342